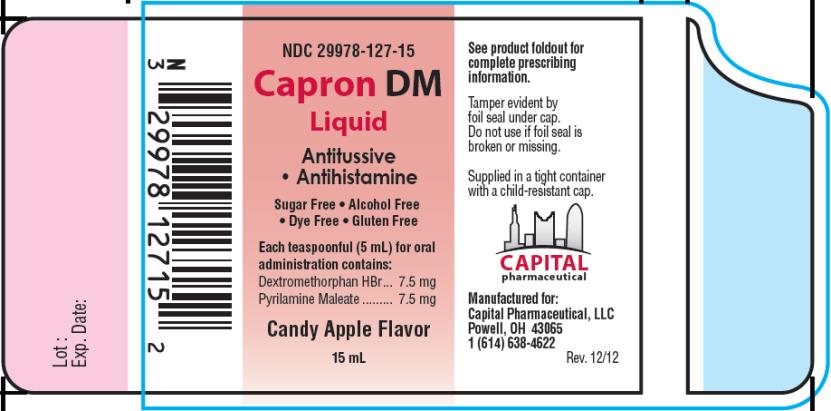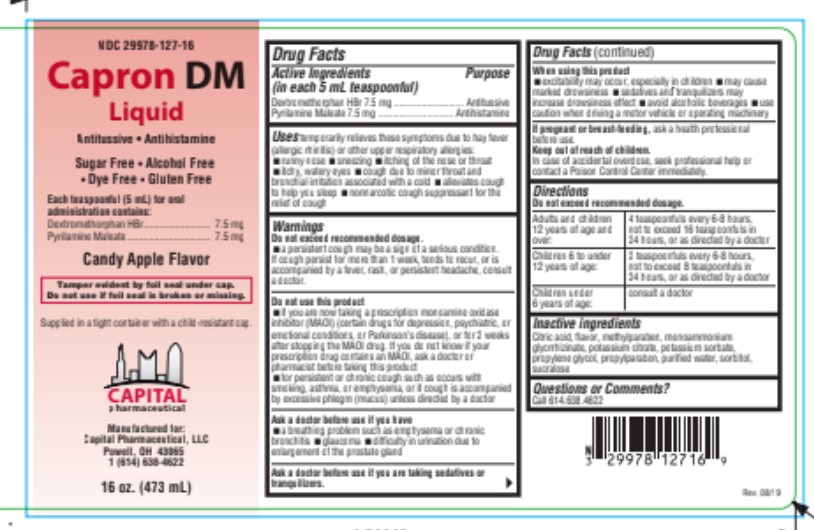 DRUG LABEL: Capron DM
NDC: 29978-127 | Form: LIQUID
Manufacturer: Capital Pharmaceutical, LLC
Category: otc | Type: HUMAN OTC DRUG LABEL
Date: 20250618

ACTIVE INGREDIENTS: DEXTROMETHORPHAN HYDROBROMIDE 7.5 mg/5 mL; PYRILAMINE MALEATE 7.5 mg/5 mL
INACTIVE INGREDIENTS: CITRIC ACID MONOHYDRATE; AMMONIUM GLYCYRRHIZATE; METHYLPARABEN; POTASSIUM CITRATE; POTASSIUM SORBATE; PROPYLPARABEN; PROPYLENE GLYCOL; WATER; SORBITOL; SUCRALOSE

Capron DM Liquid

Drug Facts

Active Ingredients

(in each 5 mL teaspoonful)

Dextromethorphan HBr 7.5 mg

Purpose

Antitussive

Active Ingredients

(in each 5 mL teaspoonful)

Pyrilamine Maleate 7.5 mg

Purpose

Antihistamine

Uses

temporarily relieves these symptoms due to hay fever (allergic rhinitis) or other upper respiratory allergies:

- runny nose
- sneezing
- itching of the nose or throat
- itchy, watery eyes
- cough due to minor throat and bronchial irritation associated with a cold
- alleviates cough to help you sleep
- nonnarcotic cough suppressant for the relief of cough

Warnings

Do not exceed recommended dosage.

- a persistent cough may be a sign of a serious condition. If cough persist for more than 1 week, tends to recur, or is accompanied by a fever, rash, or persistent headache, consult a doctor.

Do not use this product

- if you are now taking a prescription monoamine oxidase inhibitor (MAOI) (certain drugs for depression, psychiatric, or emotional conditions, or Parkinson’s disease), or for 2 weeks after stopping the MAOI drug. If you do not know if your prescription drug contains an MAOI, ask a doctor or pharmacist before taking this product
- for persistent or chronic cough such as occurs with smoking, asthma, or emphysema, or if cough is accompanied by excessive phlegm (mucus) unless directed by a doctor

Ask a doctor before use if you have

- a breathing problem such as emphysema or chronic bronchitis
- glaucoma
- difficulty in urination due to enlargement of the prostate gland

Ask a doctor before use if you are taking

sedatives or tranquilizers.

When using this product

- excitability may occur, especially in children
- may cause marked drowsiness
- sedatives and tranquilizers may increase drowsiness effect
- avoid alcoholic beverages
- use caution when driving a motor vehicle or operating machinery

If pregnant or breast-feeding,

ask a health professional before use.

Keep out of reach of children.

In case of accidental overdose, seek professional help or contact a Poison Control Center immediately.

Directions

Do not exceed recommended dosage.

Adults and children 12 years of age and over: | 4 teaspoonfuls every 6-8 hours, not to exceed 16 teaspoonfuls in 24 hours, or as directed by a doctor
Children 6 to under 12 years of age: | 2 teaspoonfuls every 6-8 hours, not to exceed 8 teaspoonfuls in 24 hours, or as directed by a doctor
Children 2 to under 6 years of age (For Professional Use Only) | 1 teaspoonful every 6-8 hours, not to exceed 4 teaspoonfuls in 24 hours, or as directed by a doctor
Children under 2 years of age: | Consult a doctor

Inactive ingredients

Citric Acid, Flavor, Magnasweet, Methyl Paraben, Potassium Citrate, Potassium Sorbate, Propyl Paraben, Propylene Glycol, Purified Water, Sorbitol, Sucralose

Questions or Comments?

Call 614.638.4622

PRINCIPAL DISPLAY PANEL

NDC 29978-127-16
Capron DM
Liquid
Candy Apple Flavor
16 oz. (473 mL)

PRINCIPAL DISPLAY PANEL

NDC 29978-127-15
Capron DM
Liquid
Candy Apple Flavor
1 5 mL